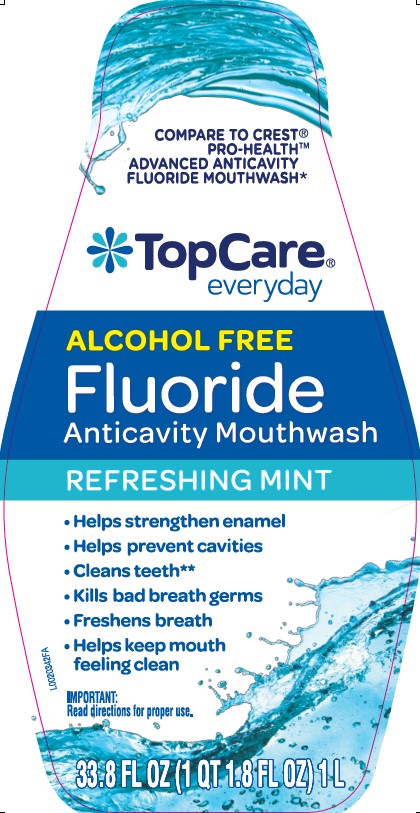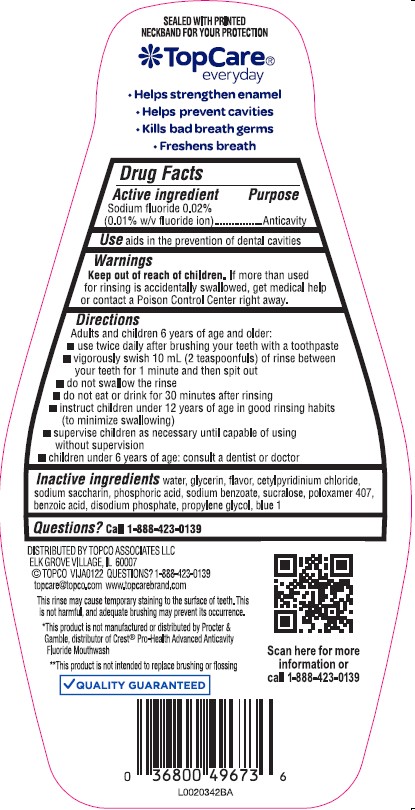 DRUG LABEL: Oral Antivavity
NDC: 76162-576 | Form: MOUTHWASH
Manufacturer: Topco Associates LLC
Category: otc | Type: HUMAN OTC DRUG LABEL
Date: 20260213

ACTIVE INGREDIENTS: SODIUM FLUORIDE 0.1 mg/1 mL
INACTIVE INGREDIENTS: WATER; GLYCERIN; CETYLPYRIDINIUM CHLORIDE; SACCHARIN SODIUM; PHOSPHORIC ACID; SODIUM BENZOATE; SUCRALOSE; POLOXAMER 407; BENZOIC ACID; SODIUM PHOSPHATE, DIBASIC, ANHYDROUS; PROPYLENE GLYCOL; FD&C BLUE NO. 1

Top Care 576.001/576AC
Whitening Anticavity Rinse

claims

SEALED WITH PRINTED NECKBAND FOR YOUR PROTECION

TopCare

everyday

- Helps strengthen enamel
- Helps prevent cavities
- Kills bad breath germs
- Freshen Breath

active ingredient

Sodium fluoride 0.02% (0.01% w/v fluoride ion)

Purpose

Anticavity

Use

aids in the prevention of dental cavities

Warnings

for this product

Keep out of reach of children.

If more than used for rinsing is accidentally swallowed, get medical help or contact a Poison Control Center right Away.

Directions

Adults and children 6 years of age and older:

- use twice daily after brushing your teeth with a toothpaste
- vigorously swish 10 mL (2 teaspoonfuls) of rinse bwtween your teeth for 1 minute then spit out
- do not swallow the rinse
- do not eat or drink for 30 minutes after rinsing
- instruct children under 12 years of age in good rinsing habits (to minimize swallowing)
- supervise children as necessary until capable of using without supervision
- children under 6 years of age: consult a dentist or doctor

Inactive ingredients

water, glycerin, flavor, cetylpyridinium chloride, sodium saccharin, phosphoric acid, sodium benzoate, sucralose, poloxamer 407, benzoic acid, disodium phosphate, propylene glycol, blue 1

Questions?

Call 1-888-423-0139

ADVERSE REACTION

DISTRIBUTED BY TOPCO ASSOCIATES LLC

ELK GROVE VILLAGE, IL 60007

©TOPCO VIJA0122 QUESTIONS? 1-888-423-0139

This rinse may cause temporary staining to the surface of teeth. This is not harmful, and adequate brushing may prevent its occurence.

*This product is not manufactured or distributed by Procter & Gamble, distributof of Crest®Pro-Health Advanced Anticavity Fluoride Mouthwash.

**This product is not intended to replace brushing or flossing.

QUALITY GUARANTEED

Scan here for more information or call 1-888-423-0139

Principal display panel

COMPARE TO CREST®PRO-HEALTH™ ADVANCED ANTICAVITY FLUORIDE MOUTHWASH*

TopCare®

everyday

ALCOHOL FREE

Fluoride

Anticavity Mouthwash

REFRESHING MINT

- Helps strengthen enamel
- Helps prevent cavities
- Cleans teeth**
- Kills bad breath germs
- Freshens breath
- Helps keep mouth feeling clean

IMPORTANT: Read directions for proper use.

33.8 FL OZ (1 QT 1.8 FL OZ) 1 L